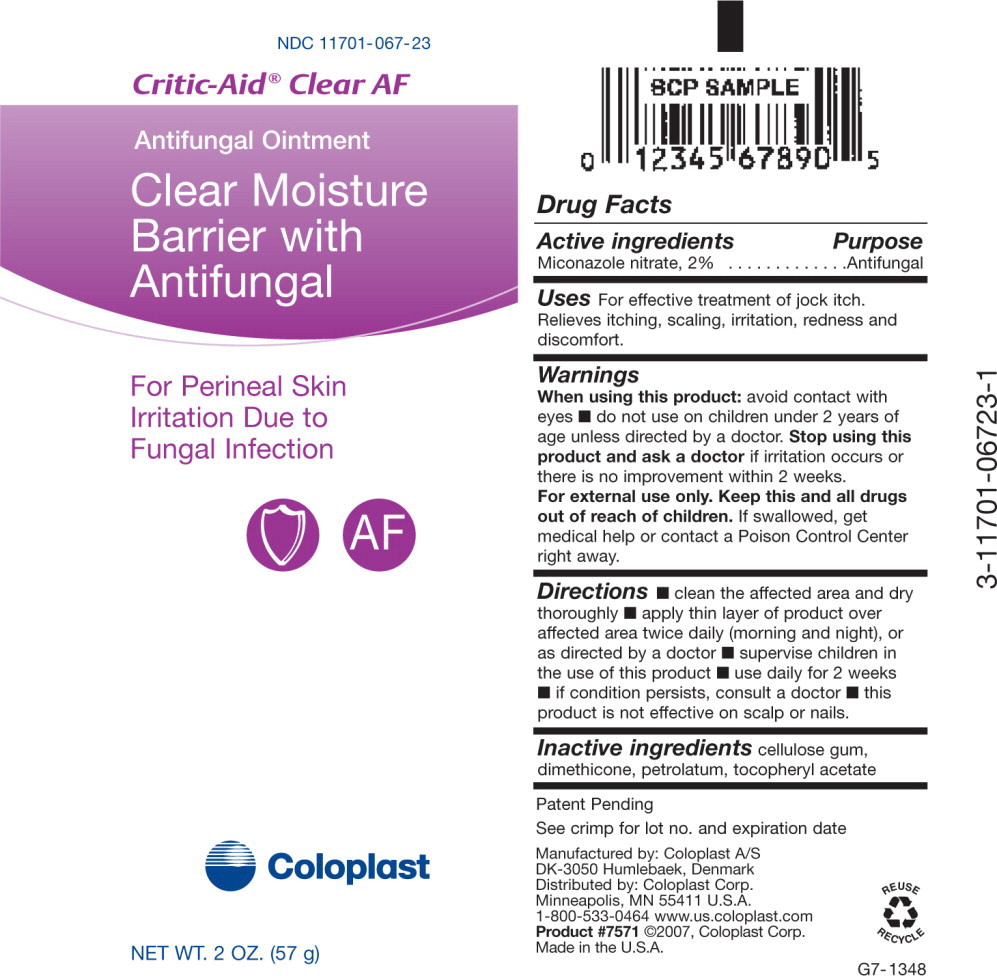 DRUG LABEL: Critic Aid Clear AF
NDC: 11701-067 | Form: OINTMENT
Manufacturer: Coloplast Manufacturing US, LLC
Category: otc | Type: HUMAN OTC DRUG LABEL
Date: 20241226

ACTIVE INGREDIENTS: MICONAZOLE NITRATE 20 mg/1 g
INACTIVE INGREDIENTS: PETROLATUM; .ALPHA.-TOCOPHEROL ACETATE, D-; DIMETHICONE; CROSCARMELLOSE SODIUM

Critic-Aid® Clear AF
Antifungal Ointment
Clear Moisture Barrier With Antifungal

For Perineal
Skin Irritation Due To
Fungal Infection

- Adheres to denuded skin
- Easy to apply and remove
- Treats topical fungal infections

Drug Facts

Active ingredient

Miconazole nitrate, 2%

Purpose

Antifungal

INDICATIONS AND USAGE

Uses For effective treatment of jock itch. Relieves itching, scaling, irritation, redness and discomfort.

Warnings

When using this product

- avoid contact with eyes
- do not use on children under 2 years of age unless directed by a doctor

STOP USE

Stop using this product and ask a doctor if irritation occurs or there is no improvement within 2 weeks.

KEEP OUT OF REACH OF CHILDREN

For external use only. Keep this and all drugs out of the reach of children. If swallowed, get medical help or contact a Poison Control Center right away.

Directions

- clean the affected area and dry thoroughly
- apply thin layer of product over affected area twice daily (morning and night), or as directed by a doctor
- supervise children in the use of this product.

Use daily for 2 weeks.

If condition persists, consult a doctor. This product is not effective on scalp or nails.

Inactive ingredients

cellulose gum, dimethicone, petrolatum, tocopheryl acetate

Patent Pending

See crimp for lot no. and expiration date

Manufactured by: Coloplast A/S DK-3050 Humlebaek, Denmark
Distributed by: Coloplast Corp. Minneapolis, MN 55411 U.S.A.
1-800-533-0464 www.us.coloplast.com Product #7572
©2007, Coloplast Corp. Made in the U.S.A.

L7-1349

PACKAGE LABEL

PRINCIPAL DISPLAY PANEL - NET WT. 5 OZ. (142g)

NDC 11701-067-14

Critic-Aid® Clear AF

Antifungal Ointment

Clear Moisture Barrier With Antifungal

For Perineal

Skin Irritation Due To

Fungal Infection

Coloplast

NET WT. 5 OZ. (142 g)